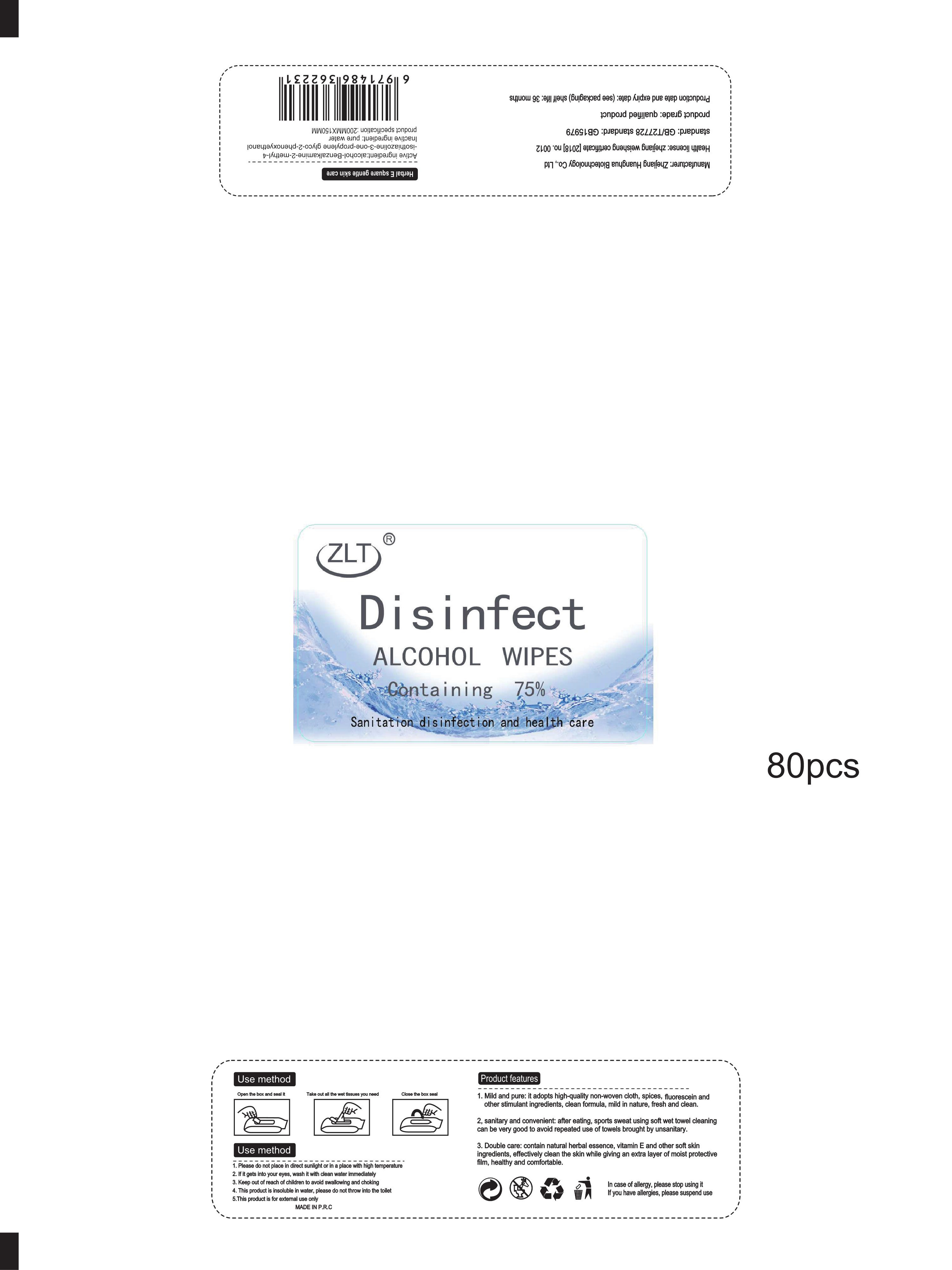 DRUG LABEL: Alcohol disinfectant wipes
NDC: 41546-013 | Form: CLOTH
Manufacturer: Zhejiang Huanghua Biological Technology Co., Ltd
Category: otc | Type: HUMAN OTC DRUG LABEL
Date: 20201207

ACTIVE INGREDIENTS: BENZALKONIUM CHLORIDE 2.475 g/80 1; METHYLISOTHIAZOLINONE 5.85 mg/80 1; PROPYLENE GLYCOL 1.98 g/80 1; PHENOXYETHANOL 0.44491 g/80 1; ALCOHOL 202.5 mL/80 1
INACTIVE INGREDIENTS: WATER

DOSAGE AND ADMINISTRATION

Please do not place in direct sunlight or in a place with high temperature

INACTIVE INGREDIENT

pure water

INDICATIONS AND USAGE

1.Open the box and seal it
2.Take out all the wet tissues you need
3.Close the box seal

ACTIVE INGREDIENT

alcohol

Benzalkamine

2-methyl-4-isothiazoline-3-one

propylene glycol

2-phenoxyethanol

keep out of reach of children

PURPOSE

Disinfection
Sterilization
No Rinseing

WARNINGS

1.Please do not place in direct sunlight or in a place with high temperature
2. lf it gets into your eyes, wash it with clean water immediately
3. Keep out of reach of children to avoid swallowing and choking
4.This product is insoluble in water, please do not throw into the toilet
5.This product is for external use only